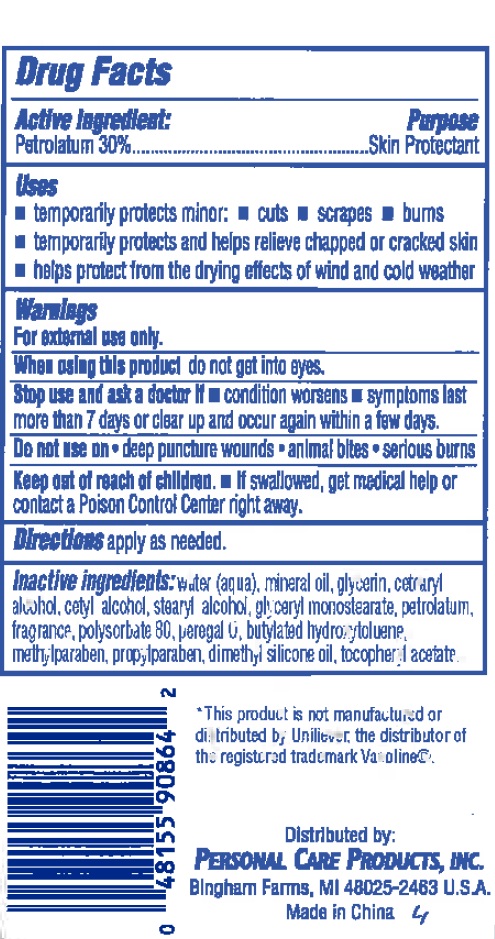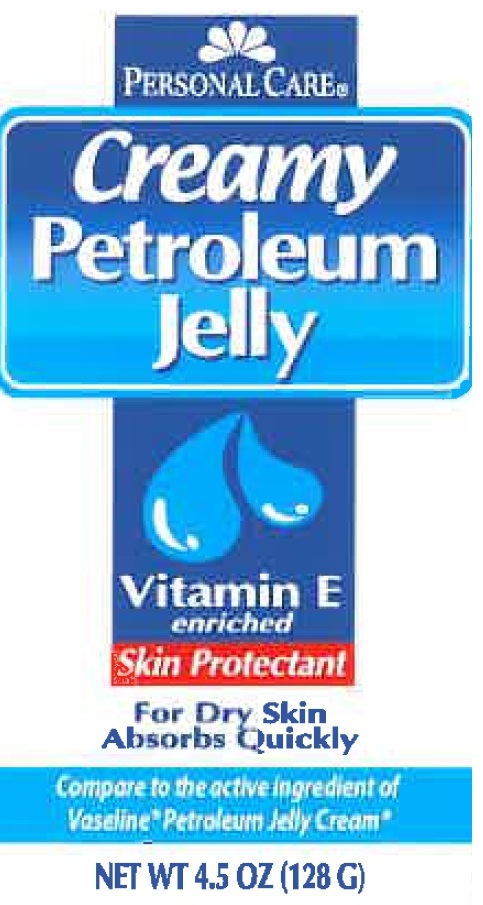 DRUG LABEL: Personal Care Creamy Petroleum Jelly
                        
NDC: 29500-0864 | Form: CREAM
Manufacturer: PERSONAL CARE PRODUCTS, LLC
Category: otc | Type: HUMAN OTC DRUG LABEL
Date: 20110825

ACTIVE INGREDIENTS: PETROLATUM 30 g/100 g
INACTIVE INGREDIENTS: WATER; MINERAL OIL; GLYCERIN; CETOSTEARYL ALCOHOL; CETYL ALCOHOL; STEARYL ALCOHOL; GLYCERYL MONOSTEARATE; PETROLATUM; POLYSORBATE 80; BUTYLATED HYDROXYTOLUENE; METHYLPARABEN; PROPYLPARABEN; .ALPHA.-TOCOPHEROL ACETATE, D-

Personal Care Creamy Petroleum Jelly

Active Ingredient

Petrolatum 30%

Purpose

Skin Protectant

Uses

Temporarily protects minor: cuts, scrapes, burns

Temporarily protects and helps relieve chapped or cracked skin.

Helps protect from the drying effects of wind and cold weather.

Warnings

For external use only

When using this product do not get into eyes.

Stop use and ask a doctor if condition worsens, symptoms last more than 7 days or clear up and occur again within a few days.

Do not use on deep puncture wounds, animal bites, serious burns.

Keep out of reach of children. If swallowed, get medical help or contact a Poison Control Center right away.

DOSAGE AND ADMINISTRATION

Directions: apply as needed.

INACTIVE INGREDIENT

Inactive Ingredients: Water (aqua), mineral oil, glycerin, cetearyl alcohol, cetyl alcohol, stearyl alcohol, glyceryl monostearate, petrolatum, fragrance, polysorbate 80, peregal O, butylated hydroxytoluene, methylparaben, propylparaben, dimethyl silicone oil, tocoopheryl acetate

PACKAGE LABEL

Personal Care

Creamy Petroleum Jelly

Vitamin E Enriched

Skin Protectant

For dry skin absorbs quickly

Compare to the active ingredient of vaseline petroleum jelly cream

net wt. 4.5oz (128g)

This product is not manufactured or distributed by unliver, the distributor of the registered trademark Vasoline

Distributed by:

Personal Care Products, Inc.

Bingham Farms, MI 48025-2463 USA

Made in China